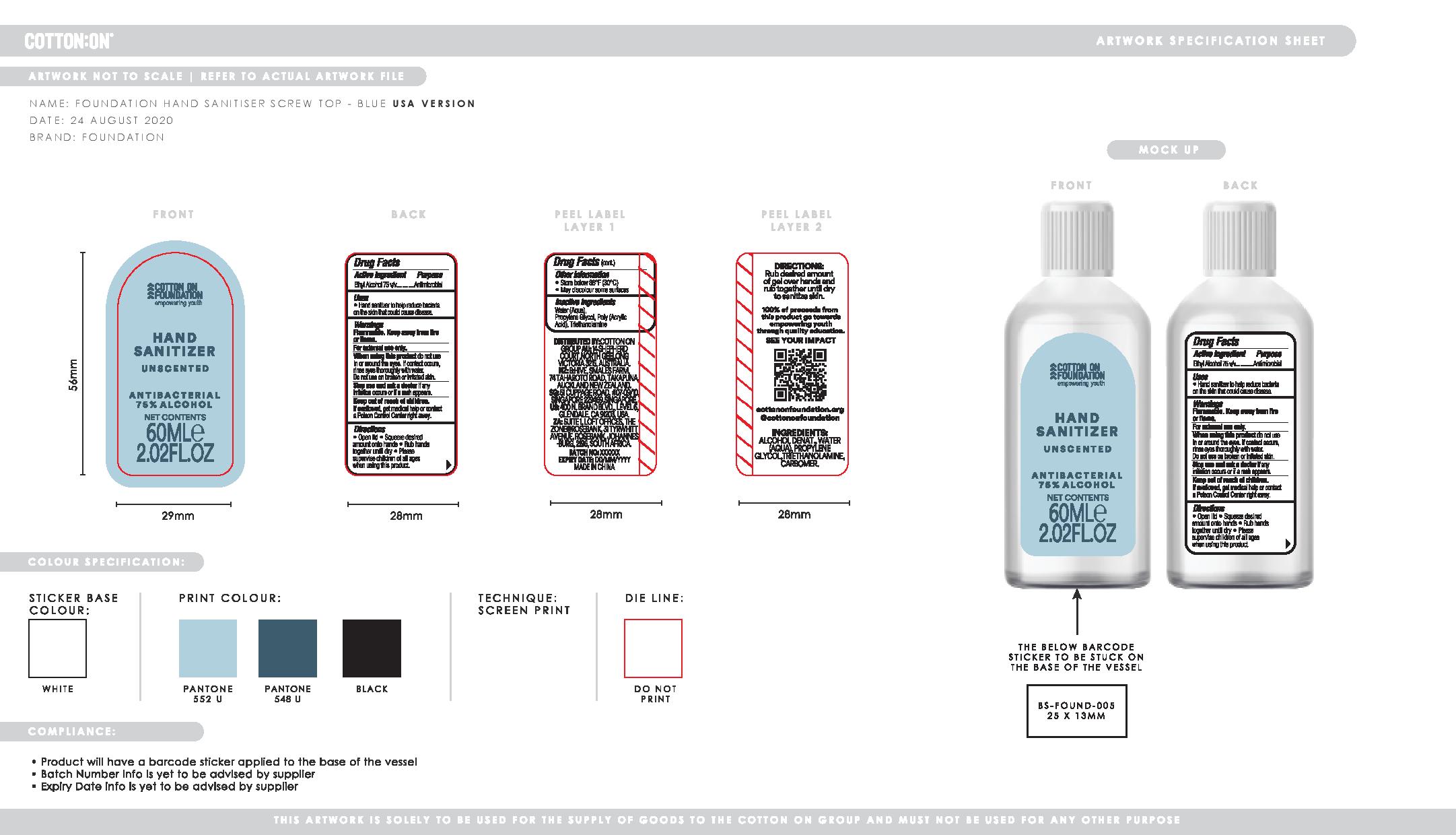 DRUG LABEL: Hand Sanitizer
NDC: 90015-001 | Form: GEL
Manufacturer: COTTON ON USA INC.
Category: otc | Type: HUMAN OTC DRUG LABEL
Date: 20200904

ACTIVE INGREDIENTS: ALCOHOL 75 mL/100 mL
INACTIVE INGREDIENTS: PROPYLENE GLYCOL 2.7 mL/100 mL; CARBOMER 940 0.25 mL/100 mL; WATER 21.8 mL/100 mL; TROLAMINE 0.25 mL/100 mL

COTTON ON HAND SANITIZER SCREW TOP USA - Charcoal

Active Ingredient(s)

Ethyl Alcohol 75% v/v. Purpose: Antimicrobial

Purpose

Purpose: Antimicrobial

Use

Hand Sanitizer to help reduce bacteria on the skin that could cause disease.

Warnings

For external use only. Flammable. Keep away from heat or flame

Do not use

When using this product do not use in or around the eyes. If contact occurs, rinse eyes thoroughly with water. Do not use on broken or irritated skin.

When using this product do not use in or around the eyes. If contact occurs, rinse eyes thoroughly with water. Do not use on broken or irritated skin.

Stop use and ask a doctor if irritation or rash occurs.

Keep out of reach of children. If swallowed, get medical help or contact a Poison Control Center right away.

Stop use and ask a doctor if irritation or rash occurs.

Keep out of reach of children. If swallowed, get medical help or contact a Poison Control Center right away.

Directions

- Open lid
- Squeeze desired amount onto hands
- Rub Hands together until dry
- Please supervise children of all ages when using this product.

Other information

- Store below 86F (30C)
- May discolour some surfaces

Inactive ingredients

Water (aqua), Propylene Glycol, Poly (Acrylic Acid), Triethanolamine

Package Label - Principal Display Panel

Hand Sanitizer

Unscented

Antimicrobial

75% Alcohol

Net Contents

60 mL

2.02FL.OZ